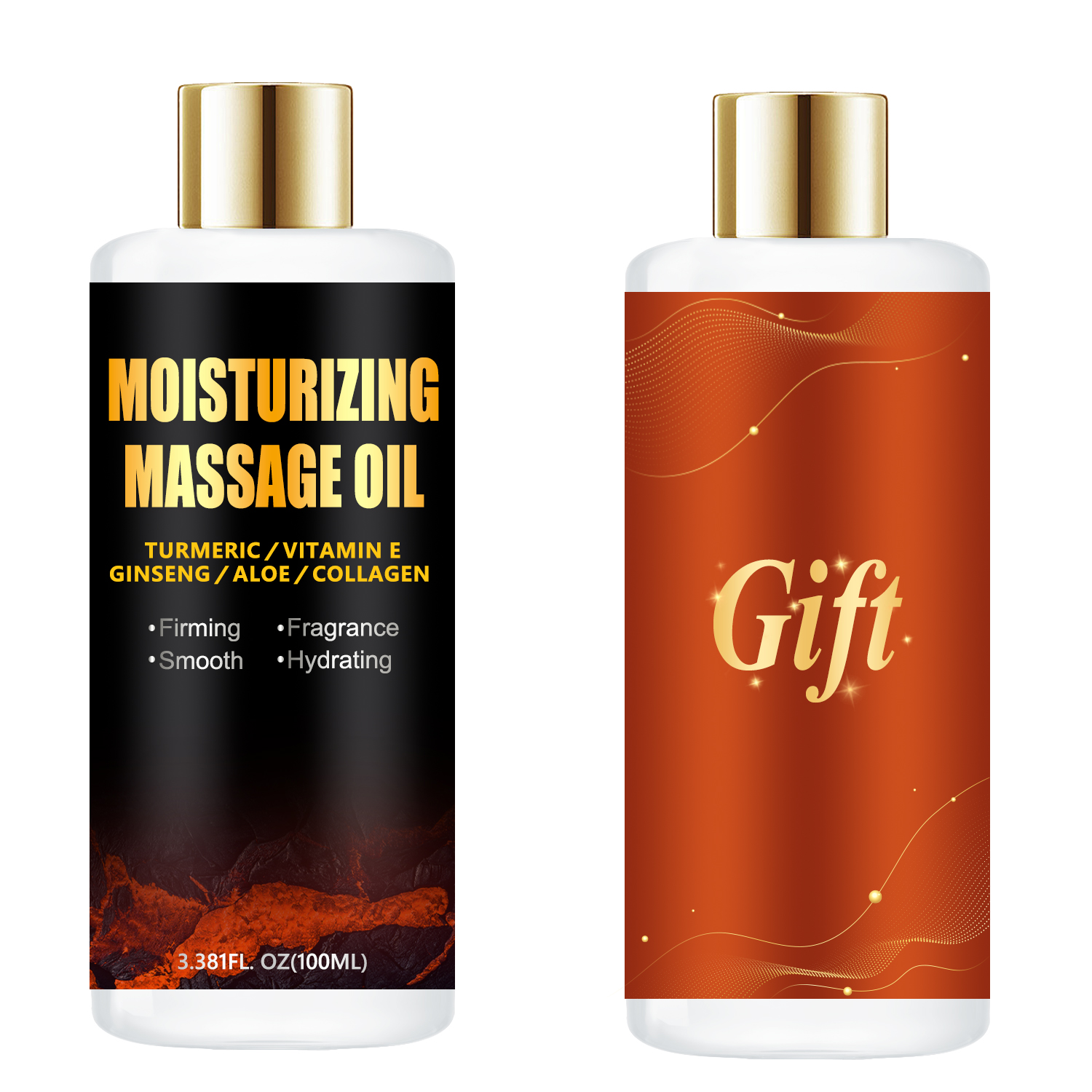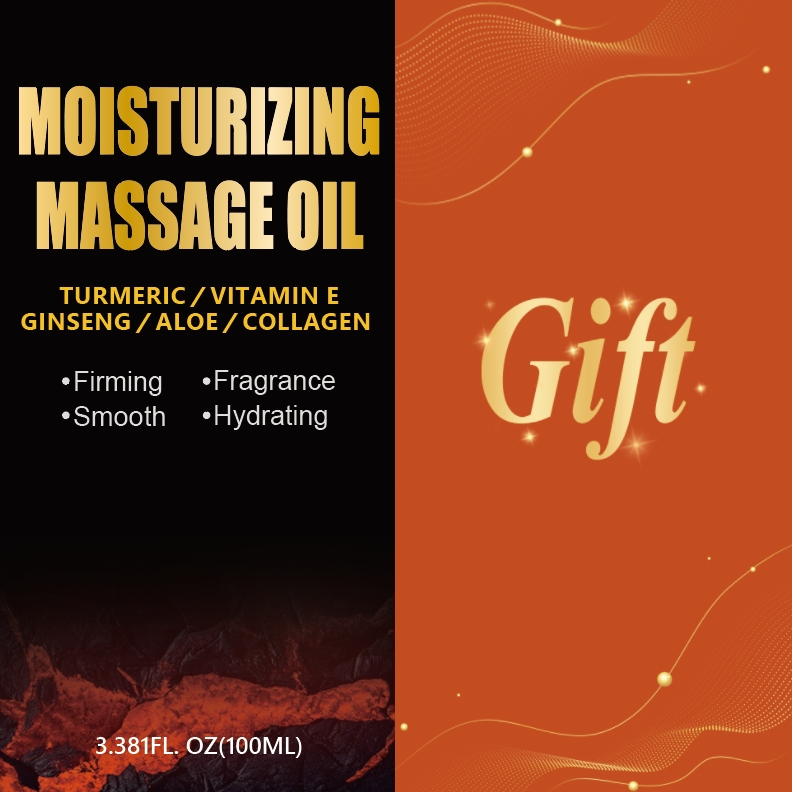 DRUG LABEL: Moisturizing Oil
NDC: 84025-229 | Form: OIL
Manufacturer: Guangzhou Yanxi Biotechnology Co., Ltd
Category: otc | Type: HUMAN OTC DRUG LABEL
Date: 20241022

ACTIVE INGREDIENTS: GLYCERIN 3 mg/100 mL; ALOE BARBADENSIS LEAF EXTRACT 5 mg/100 mL
INACTIVE INGREDIENTS: WATER

DOSAGE AND ADMINISTRATION

use as normal body oil

WARNINGS

keep out of children

INACTIVE INGREDIENT

AQUA

INDICATIONS AND USAGE

for daily body care

keep out of children

PURPOSE

Lightweight body oil helps dry skin pampers your skin as a sheer moisturizer that instantly vanishes and absorbs quickly into skin, providing essential hydration while locking in moisture without leaving a greasy feel